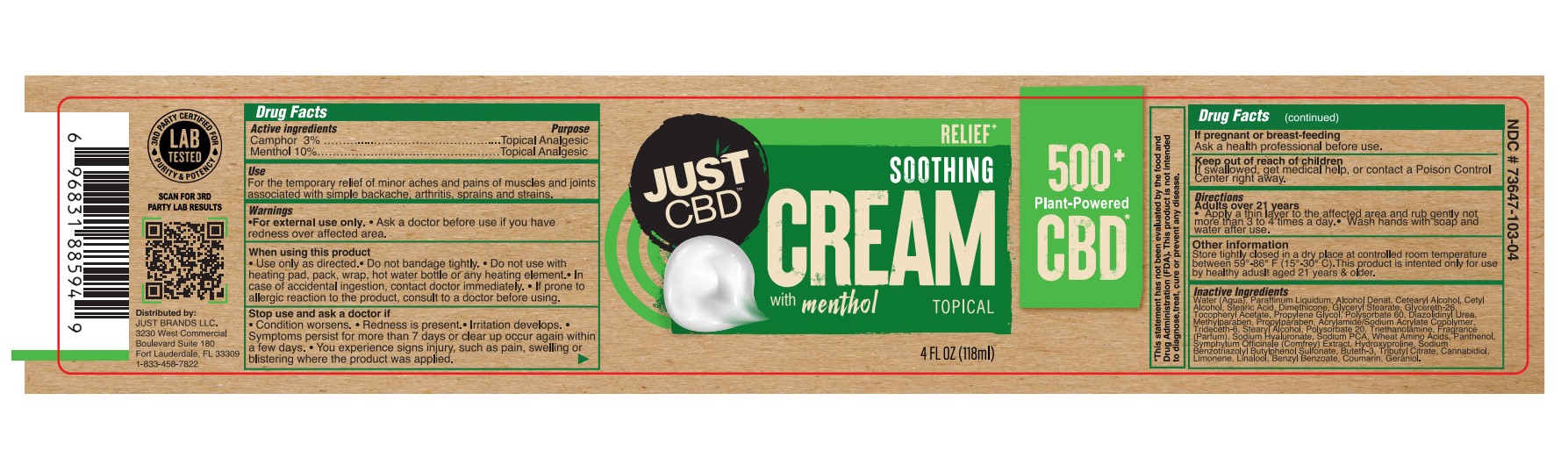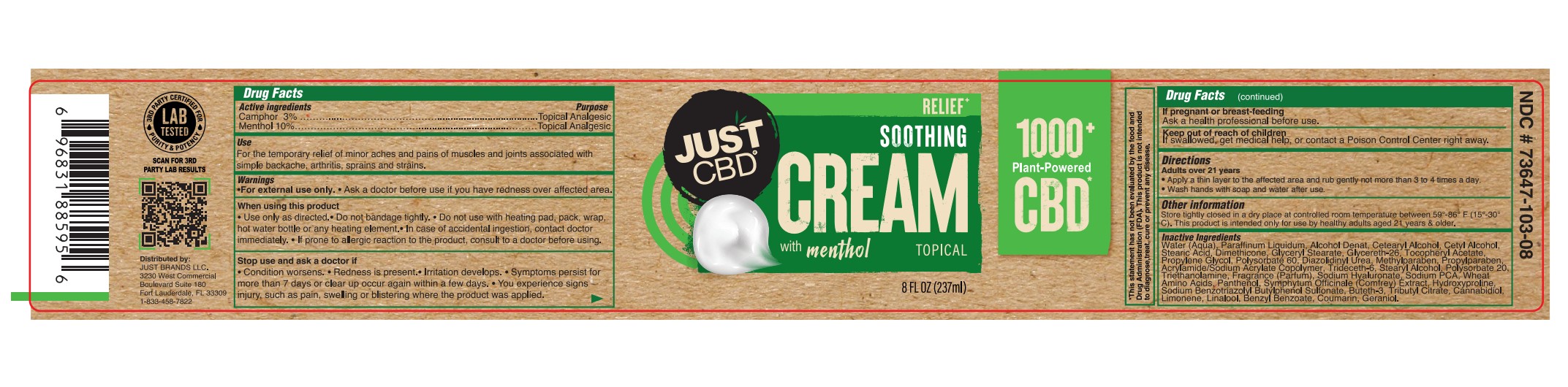 DRUG LABEL: JUST CBD SOOTHING
NDC: 73647-103 | Form: CREAM
Manufacturer: Just Brands LLC
Category: otc | Type: HUMAN OTC DRUG LABEL
Date: 20251117

ACTIVE INGREDIENTS: MENTHOL, UNSPECIFIED FORM 10 g/100 mL; CAMPHOR (SYNTHETIC) 3 g/100 mL
INACTIVE INGREDIENTS: PROPYLENE GLYCOL; LINALOOL, (+/-)-; WATER; MINERAL OIL; CETOSTEARYL ALCOHOL; PROPYLPARABEN; CANNABIDIOL; TROLAMINE; STEARIC ACID; GLYCERYL STEARATE SE; GLYCERETH-26; DIAZOLIDINYL UREA; METHYLPARABEN; TRIDECETH-6; GERANIOL; COUMARIN; COMFREY LEAF; BUTETH-3; AMINO ACIDS, WHEAT; CETYL ALCOHOL; .ALPHA.-TOCOPHEROL ACETATE; SODIUM PYRROLIDONE CARBOXYLATE; HYDROXYPROLINE; TRIBUTYL CITRATE; DIMETHICONE 1000; POLYSORBATE 60; STEARYL ALCOHOL; POLYSORBATE 20; HYALURONATE SODIUM; ALCOHOL; SODIUM BENZOTRIAZOLYL BUTYLPHENOL SULFONATE; PANTHENOL; LIMONENE, (+)-; BENZYL BENZOATE

73647-103-04
73647-103-08

ACTIVE INGREDIENT

Camphor 3%

Menthol 10%

PURPOSE

Topical Analgesic

USE

For the temporary relief of minor aches and pains of muscles and joints associated with simple backache, arthritis, sprains and strains.

WARNINGS

For external use only.

Ask a doctor before use if you have redness over affected area.

WHEN USING

• Use only as directed.

• Do not bandage tightly.

• Do not use with heating pad, pack, wrap, hot water bottle or any heating element.

• In case of accidental ingestion, contact doctor immediately.

• If prone to allergic reaction to the product, consult to a doctor before using.

STOP USE

• Condition worsens.

• Redness is present.

• Irritation develops.

• Symptoms persist for more than 7 days or clear up occur again within a few days.

• You experience signs injury, such as pain, swelling or blistering where the product was applied.

KEEP OUT OF REACH OF CHILDREN

If swallowed, get medical help or contact a Poison Control Center right away.

If pregnant or breast-feeding
Ask a health professional before use.

DIRECTIONS

Adults over 21 years
• Apply a thin layer to the affected area and rub gently not more than 3 to 4 times a day.
• Wash hands with soap and water after use.

OTHER SAFETY INFORMATION

Store tighly closed in a dry place at controlled room temperature between 59°-86° F (15°-30° C).

This product is intended only for use by healthy adults aged 21 years & older.

INACTIVE INGREDIENT

Water (Aqua), Paraffinum Liquidum, Alcohol Denat, Cetearyl Alcohol, Cetyl Alcohol, Stearic Acid, Dimethicone, Glyceryl Stearate, Glycereth-26, Tocopheryl Acetate, Propylene Glycol, Polysorbate 60, Diazolidinyl Urea, Methylparaben, Propylparaben, Acrylamide/Sodium Acrylate Copolymer, Trideceth-6, Stearyl Alcohol, Polysorbate 20, Triethanolamine, Fragrance (Parfum), Sodium Hyaluronate, Sodium PCA, Wheat Amino Acids, Panthenol, Symphytum Officinale (Comfrey) Extract, Hydroxyproline, Sodium Benzotriazolyl Butylphenol Sulfonate, Buteth-3, Tributyl Citrate, Cannabidiol, Limonene, Linalool, Benzyl Benzoate, Coumarin, Geraniol.